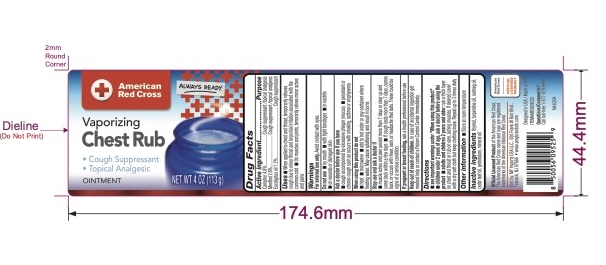 DRUG LABEL: Chest Rub
NDC: 51628-4242 | Form: OINTMENT
Manufacturer: MY IMPORTS USA LLC
Category: otc | Type: HUMAN OTC DRUG LABEL
Date: 20250821

ACTIVE INGREDIENTS: CAMPHOR (SYNTHETIC) 4.8 g/100 g; EUCALYPTUS OIL 1.2 g/100 g; MENTHOL 2.6 g/100 g
INACTIVE INGREDIENTS: CEDAR LEAF OIL; NUTMEG OIL; THYMOL; TURPENTINE OIL; PETROLATUM; MINERAL OIL

American Red Cross Chest Rub

Drug Facts

Active ingredients

Camphor 4.8%
Menthol 2.6%

Eucalyptus oil 1.2%

Purpose

Cough suppressant & Topical Analgesic

Uses

- when applied to chest and throat, temporarily relieves cough due to minor throat and bronchial irritation associated with the common cold
- when applied to muscles and joints, temporarily relieves minor aches and pains of muscles and joints

Warnings

For external use only;avoid contact with eyes.

Do not use

- by mouth
- with tight bandages
- in nostrils
- on wounds or damaged skin

Ask a doctor before use if you have

- cough that occurs with too much phlegm (mucus)
- persistent or chronic cough such as occurs with smoking, asthma or emphysema

When using this product, do not

- heat
- microwave
- add to hot water or any container where heating water.
  May cause splattering and result in burns.

Stop use and ask a doctor if

- muscle aches and pains persist more than 7 days or clear up and come back with a few days
- cough lasts for more than 7 days, comes back, or occurs with fever, rash, or persistent headache. A persistent cough may be a sign of a serious condition.

PREGNANCY OR BREAST FEEDING

If pregnant or breast-feeding,ask a health professional before use.

Keep out of reach of children.If swallowed, get medical help or contact a Poison Control Center right away.

Directions

see important warnings under " When using this product"

- Children under 2 years of age, ask a doctor before using the product
- Adults and Children 2 years and older: rub a thick layer on throat & chest or rub on sore, aching muscles. If desired cover with a dry soft cloth but keep clothing loose. Repeat up to 3 times daily

Other information

- store at room temperature

Inactive ingredients

Petrolatum, Mineral Oil, Nutmeg Oil, Turpentine Oil, Thymol, Cedar Leaf Oil